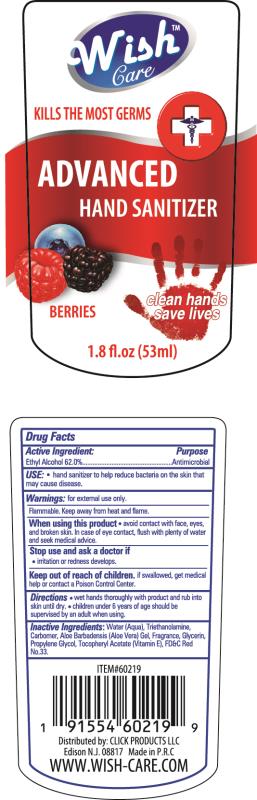 DRUG LABEL: Advanced Hand Sanitizer
NDC: 71611-014 | Form: GEL
Manufacturer: Click Products LLC
Category: otc | Type: HUMAN OTC DRUG LABEL
Date: 20200323

ACTIVE INGREDIENTS: ALCOHOL 62 g/53 mL
INACTIVE INGREDIENTS: ALOE VERA FLOWER; D&C RED NO. 33; GLYCERIN; COCETH-7; CARBOXYMETHYL FRAGMENT; PPG-1-PEG-9 LAURYL GLYCOL ETHER; SODIUM HYDROXIDE; WATER

Advanced Hand Sanitizer -Berries

Active Ingredient

Alcohol............... 62%

PURPOSE

Antimicrobial

Keep out of reach of children.

Warnings

- for external use only-hands.
- keep out of eyes. avoid contact with broken skin.
- stop use and ask a Doctor if irritation or redness develops.
- do not inhale or ingest. if swallowed, get medical help or contact a poison control center right away.
- flamable. keep away from heat

Directions

- Rub a dime sized drop into hands.
- For children under 6 use under adult supervision.

Inactive Ingredients

water, glycerin, coceth-7, PPG-1-PEG-9 lauryl glycol ether, carbomer, PEG-40 hydrogenated castor oil, fragrance (parfum).

May Contain

Red 40 (CI 16035), Red 33 (CI 17200), Blue 1 (CI 42090), Yellow 5 (CI 19140).

INDICATIONS AND USAGE

Hand Sanitizer